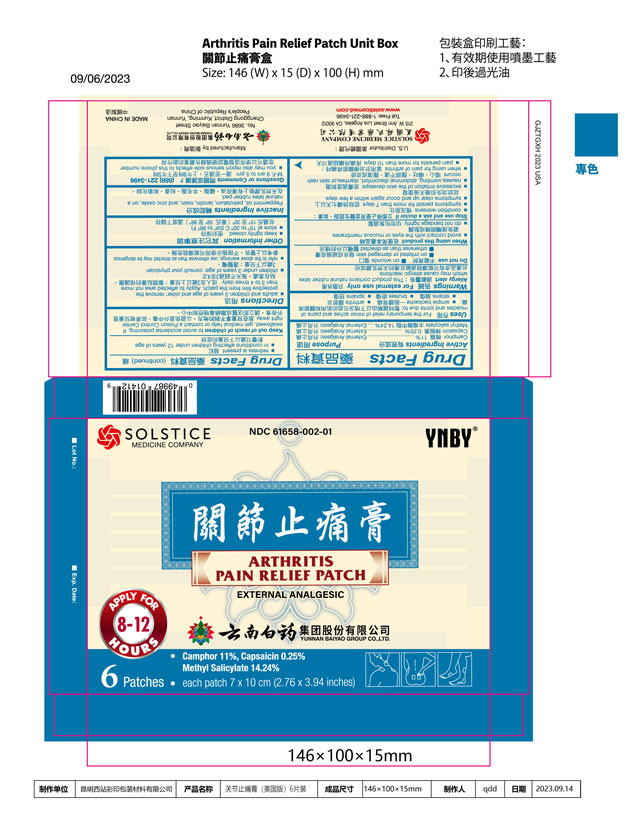 DRUG LABEL: ARTHRITIS PAIN RELIEF
NDC: 61658-002 | Form: PATCH
Manufacturer: YUNNAN BAIYAO GROUP CO., LTD.
Category: otc | Type: HUMAN OTC DRUG LABEL
Date: 20250721

ACTIVE INGREDIENTS: CAMPHOR (SYNTHETIC) 128.04 mg/1 1; CAPSAICIN 2.88 mg/1 1; METHYL SALICYLATE 168.03 mg/1 1
INACTIVE INGREDIENTS: PEPPERMINT OIL; PETROLATUM; LANOLIN; ROSIN; ZINC OXIDE; NATURAL LATEX RUBBER

DRUG FACTS

Active ingredients
Camphor 11%
Capsaicin 0.25%
Methyl salicylate 14.24%

Purpose
External analgesic
External analgesic
External analgesic

INDICATIONS AND USAGE

UsesFor the temporary relief of minor aches and pains of muscles and joints due to:
simple backache
arthritis
strains
bruises
sprains

Warnings

For external use only

Allergy alert:This product contains natural rubber latex which may cause allergic reactions

Do not use
on irritated or damaged skin
on wounds
otherwise than as directed

When using this product
avoid contact with the eyes or mucous membranes
do not bandage tightly

Stop use and ask a doctor ifcondition worsens
symptoms persist for more than 7 days
symptoms clear up and occur again within a few days
excessive irritation of the skin develops
nausea, vomiting, abdominal discomfort, diarrhea, or skin rash occurs
when using for pain of arthritis:
pain persists for more than 10 days
redness is present
in conditions affecting children under 12 years of age

KEEP OUT OF REACH OF CHILDREN

Keep out of reach of childrento avoid accidental poisoning. If swallowed, get medical help or contact a Poison Control Center right away.

Directions
adults and children 3 years of age and older: remove the attached film from the plaster. Apply to affected area not more than 3 to 4 times daily
children under 3 years of age: consult your physician
refer to the above warnings; use otherwise than as directed may be dangerous

Other information
keep tightly closed
store at 15 to 30C (59 to 86F)

INACTIVE INGREDIENT

Inactive ingredientsPeppermint oil, petrolatum, lanolin, rosin, and zinc oxide, on a natural latex rubber pad.

Questions or comments?(888) 221-3496 M-F 9 am to 5 pm
you may also report serious side effects to this phone number

PACKAGE LABEL

ARTHRITIS PAIN RELIEF PATCH

External Analgesic

NDC 61658-002-01

Camphor 11%, Capsaicin 0.25%, Methyl Salicylate 14.24%

6 Patches
Each Patch 7 x 10 cm (2.76 x 3.94 in)